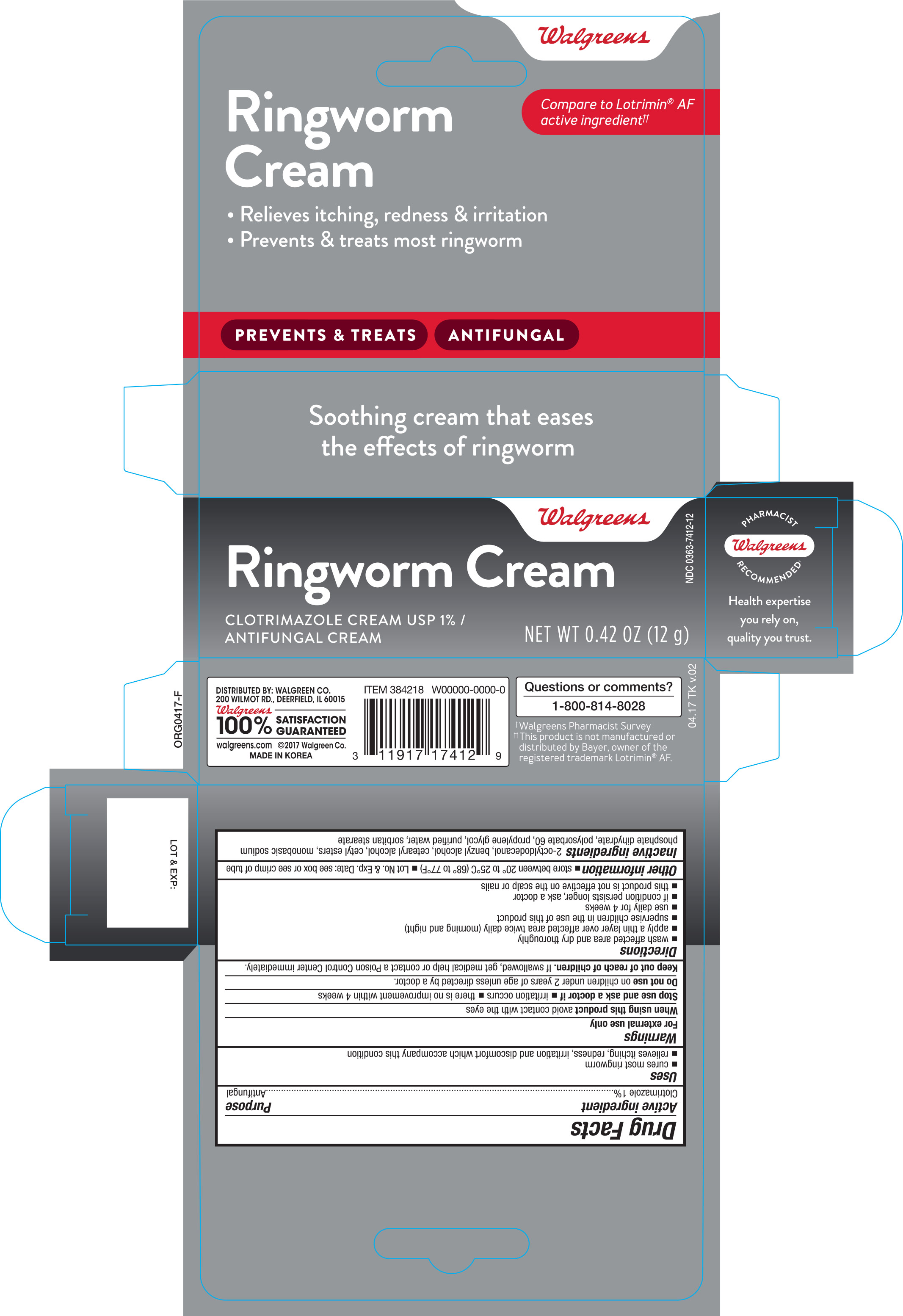 DRUG LABEL: Walgreens Clotrimazole Antifungal
NDC: 0363-7412 | Form: CREAM
Manufacturer: Walgreen Company
Category: otc | Type: HUMAN OTC DRUG LABEL
Date: 20181211

ACTIVE INGREDIENTS: CLOTRIMAZOLE 1 g/100 g
INACTIVE INGREDIENTS: OCTYLDODECANOL; BENZYL ALCOHOL; CETYL ESTERS WAX; SODIUM PHOSPHATE, MONOBASIC, DIHYDRATE; POLYSORBATE 60; PROPYLENE GLYCOL; WATER; SORBITAN MONOSTEARATE

Walgreens Clotrimazole Antifungal Ringworm Cream 0.42oz (384218, 2018)

Active ingredient Purpose

Clotrimazole 1%...................................................................... Antifungal

Uses

- cures most ringworm
- relieves itching, redness, irritation and discomfort which accompany this condition

Warnings

For external use only

When using this product avoid contact with the eyes

Stop use and ask a doctor if

- irritation occurs
- there is no improvement within 4 weeks

Do not use on children under 2 years of age unless directed by a doctor.

Keep out of reach of children. If swallowed, get medical help or contact a Poison Control Center immediately.

Directions

- wash affected area and dry thoroughly
- apply a thin layer over affected area twice daily (morning and night)
- supervise children in the use of this product
- use daily for 4 weeks
- if condition persists longer, ask a doctor
- this product is not effective on the scalp or nails

Other information

- store between 20° to 25°C (68° to 77°F)
- Lot No. & Exp. Date: see box or see crimp of tube

Inactive ingredients

2-octyldodecanol, benzyl alcohol, cetearyl alcohol, cetyl esters, monobasic sodium, phosphate dihydrate, polysorbate 60, propylene glycol, purified water, sorbitan stearate

DOSAGE AND ADMINISTRATION

Distributed by:

Walgreen Co.

200 Wilmot Rd.

Deerfield, IL 60015

Made in Korea